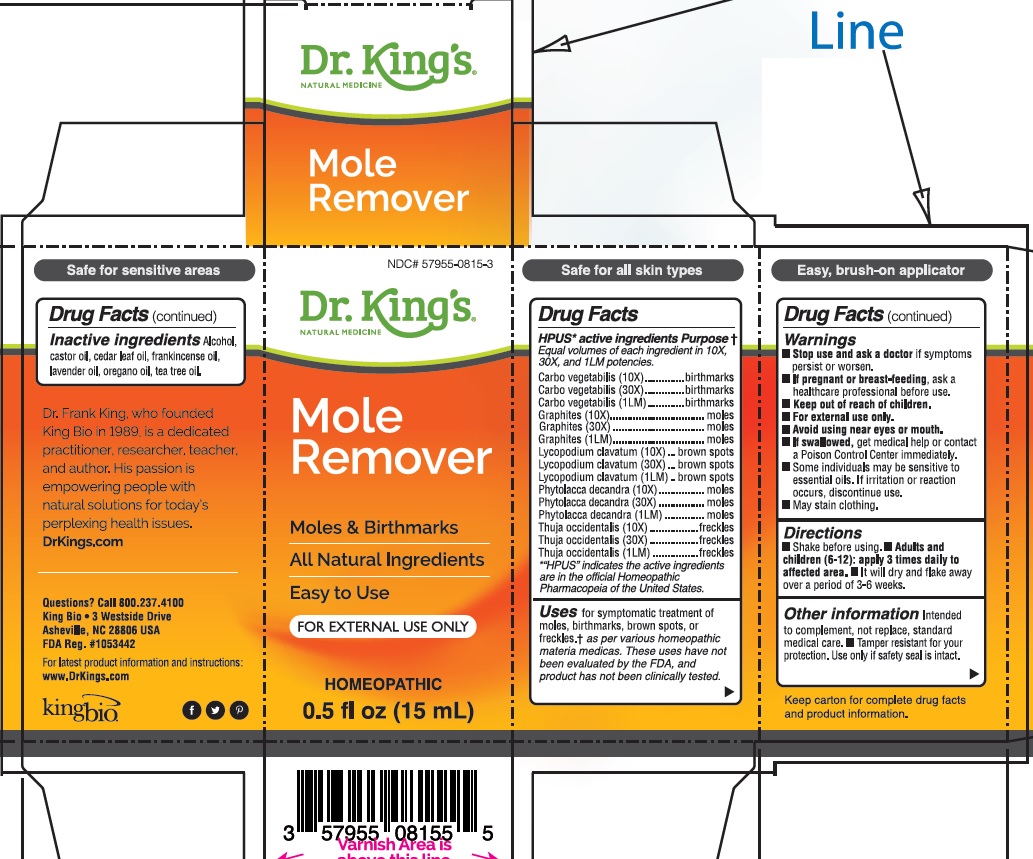 DRUG LABEL: Mole Remover
NDC: 57955-0815 | Form: LIQUID
Manufacturer: King Bio Inc.
Category: homeopathic | Type: HUMAN OTC DRUG LABEL
Date: 20200508

ACTIVE INGREDIENTS: CARBO ANIMALIS 10 [hp_X]/15 mL; GRAPHITE 10 [hp_X]/15 mL; LYCOPODIUM CLAVATUM SPORE 10 [hp_X]/15 mL; PHYTOLACCA AMERICANA ROOT 10 [hp_X]/15 mL; THUJA OCCIDENTALIS LEAFY TWIG 10 [hp_X]/15 mL
INACTIVE INGREDIENTS: ALCOHOL; CASTOR OIL; CEDAR LEAF OIL; FRANKINCENSE OIL; LAVENDER OIL; OREGANO LEAF OIL; TEA TREE OIL

Mole Remover™

ACTIVE INGREDIENT

HPUS active ingredients: Equal volumes of each ingredient in 10X, 30X, and LM1 potencies. Carbo veg, Graphites, Lycopodium, Phytolacca, Thuja occ. "HPUS" indicates the active ingredients are in the official Homeopathic Pharmacopeia of the United States.

INDICATIONS AND USAGE

Uses † for symptomatic treatment of moles, birthmarks, brown spots, or freckles. † as per various homeopathic materia medicas. These uses have not been evaluated by the FDA, and product has not been clinically tested.

Warnings

- For external use only.
- Avoid using near eyes or mouth.
- If swallowed, get medical help or contact a Poison Control Center immediately.
- Some individuals may be sensitive to essential oils. If irritation or reaction occurs, discontinue use.
- May stain clothing.

Stop use and ask a doctor if symptoms persist or worsen.

PREGNANCY OR BREAST FEEDING

If pregnant or breast-feeding, ask a healthcare professional before use.

Keep out of reach of children.

Directions

- Shake before using.
- Adults and children (6-12): apply 3 times daily to affected area.
- It will dry and flake away over a period of 3-6 weeks.

Other information:

- Intended to complement, not replace, standard medical care.
- Tamper resistant for your protection. Use only if safety seal is intact.

INACTIVE INGREDIENT

Inactive Ingredients: Alcohol, castor oil, cedar leaf oil, frankincense oil, oregano oil, lavender oil, tea tree oil.

HPUS active ingredients Purpose

Equal volumes of each ingredient in 10X, 30X, and LM1 potencies.

Carbo vegetabilis (10X) birthmarks
Carbo vegetabilis (30X) birthmarks
Carbo vegetabilis (1LM) birthmarks
Graphites (10X)......................... moles
Graphites (30X)......................... moles
Graphites (1LM) ........................ moles
Lycopodium clavatum (10X)
brown spots
Lycopodium clavatum (30X)
brown spots
Lycopodium clavatum (1LM)
brown spots
Phytolacca decandra (10X)........ moles
Phytolacca decandra (30X)........ moles
Phytolacca decandra (1LM) moles
Thuja occidentalis (10X) freckles
Thuja occidentalis (30X) freckles
Thuja occidentalis (1LM) .........freckles
*“HPUS” indicates the active ingredients
are in the official Homeopathic
Pharmacopeia of the United States.

Questions? Call 866.298.2740
King Bio, Inc. • 3 Westside Drive
Asheville, NC 28806 USA
FDA Reg. #1053442

For latest product information and instructions: www.DrKings.com